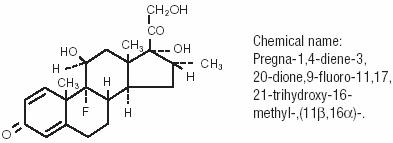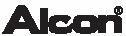 DRUG LABEL: Unknown
Manufacturer: ALCON LABORATORIES, INC.
Category: prescription | Type: Human Prescription Drug Label
Date: 20060821

Maxidex® 0.1%
(dexamethasone ophthalmic suspension)
Sterile

DESCRIPTION

MAXIDEX® 0.1% (dexamethasone ophthalmic suspension) is an adrenocortical steroid prepared as a sterile topical ophthalmic suspension. The active ingredient is represented by the chemical structure:

Each mL contains

Active: dexamethasone 0.1%. Preservative: benzalkonium chloride 0.01%. Vehicle: hypromellose 0.5%. Inactives: sodium chloride, dibasic sodium phosphate, polysorbate 80, edetate disodium, citric acid and/or sodium hydroxide (to adjust pH), purified water.

CLINICAL PHARMACOLOGY

Dexamethasone suppresses the inflammatory response to a variety of agents and it probably delays or slows healing.

INDICATIONS AND USAGE

Steroid responsive inflammatory conditions of the palpebral and bulbar conjunctiva, cornea, and anterior segment of the globe such as allergic conjunctivitis, acne rosacea, superficial punctuate keratitis, herpes zoster keratitis, iritis, cyclitis, selected infective conjunctivitides when the inherent hazard of steroid use is accepted to obtain an advisable diminution in edema and inflammation; corneal injury from chemical, radiation, or thermal burns, or penetration of foreign bodies.

CONTRAINDICATIONS

Contraindicated in epithelial herpes simplex (dendritic keratitis), vaccinia, varicella, and most other viral diseases of the cornea and conjunctiva; tuberculosis of the eye; fungal disease of ocular structures; and in those persons who have shown hypersensitivity to any component of this preparation.

WARNINGS

Prolonged use may result in ocular hypertension and/or glaucoma, with damage to the optic nerve, defects in visual acuity and fields of vision, and posterior subcapsular cataract formation. Prolonged use may suppress the host response and thus increase the hazard of secondary ocular infections. In those diseases causing thinning of the cornea or sclera, perforations have been known to occur with the use of topical corticosteroids. In acute purulent conditions of the eye, corticosteroids may mask infection or enhance existing infection. If these products are used for 10 days or longer, intraocular pressure should be routinely monitored even though it may be difficult in children and uncooperative patients.

Employment of corticosteroid medication in the treatment of herpes simplex other than epithelial herpes simplex keratitis, in which it is contraindicated, requires great caution; periodic slit-lamp microscopy is essential.

PRECAUTIONS

General

FOR TOPICAL OPHTHALMIC USE ONLY. The possibility of persistent fungal infections of the cornea should be considered after prolonged corticosteroid dosing.

Information for Patients

Do not touch dropper tip to any surface, as this may contaminate the contents. The preservative in MAXIDEX® (dexamethasone ophthalmic suspension), benzalkonium chloride, may be absorbed by soft contact lenses. MAXIDEX® (dexamethasone ophthalmic suspension) should not be administered while wearing soft contact lenses.

Carcinogenesis, Mutagenesis, Impairment of Fertility

Long-term animal studies have not been performed to evaluate the carcinogenic potential or the effect on fertility of MAXIDEX® dexamethasone ophthalmic suspension).

Pregnancy

Pregnancy Category C

Dexamethasone has been shown to be teratogenic in mice and rabbits following topical ophthalmic application in multiples of the therapeutic dose.

In the mouse, corticosteroids produce fetal resorptions and a specific abnormality, cleft palate. In the rabbit, corticosteroids have produced fetal resorptions and multiple abnormalities involving the head, ears, limbs, palate, etc.

There are no adequate or well-controlled studies in pregnant women. MAXIDEX® (dexamethasone ophthalmic suspension) should be used during pregnancy only if the potential benefit to the mother justifies the potential risk to the embryo or fetus. Infants born of mothers who have received substantial doses of corticosteroids during pregnancy should be observed carefully for signs of hypoadrenalism.

Nursing Mothers

Systemically administered corticosteroids appear in human milk and could suppress growth, interfere with endogenous corticosteroid production, or cause other untoward effects. It is not known whether topical administration of corticosteroids could result in sufficient systemic absorption to produce detectable quantities in human milk. Because many drugs are excreted in human milk, caution should be exercised when MAXIDEX® (dexamethasone ophthalmic suspension) is administered to a nursing woman.

Pediatric Use

Safety and effectiveness in pediatric patients have not been established.

Geriatric Use

No overall differences in safety or effectiveness have been observed between elderly and younger patients.

ADVERSE REACTIONS

Glaucoma with optic nerve damage, visual acuity and field defects; cataract formation; secondary ocular infection following suppression of host response; and perforation of the globe may occur.

DOSAGE AND ADMINISTRATION

SHAKE WELL BEFORE USING. One or two drops topically in the conjunctival sac(s). In severe disease, drops may be used hourly, being tapered to discontinuation as the inflammation subsides. In mild disease, drops may be used up to four to six times daily.

HOW SUPPLIED

MAXIDEX® (dexamethasone ophthalmic suspension) in plastic DROP-TAINER® dispensers:

5 mL NDC 0998-0615-05

15 mL NDC 0998-0615-15

STORAGE

Store upright at 8°-27°C (46°-80°F).

Rx Only

© 2003 Alcon, Inc.

ALCON LABORATORIES, INC.
Fort Worth, Texas 76134 USA
Printed in USA

340907-0803